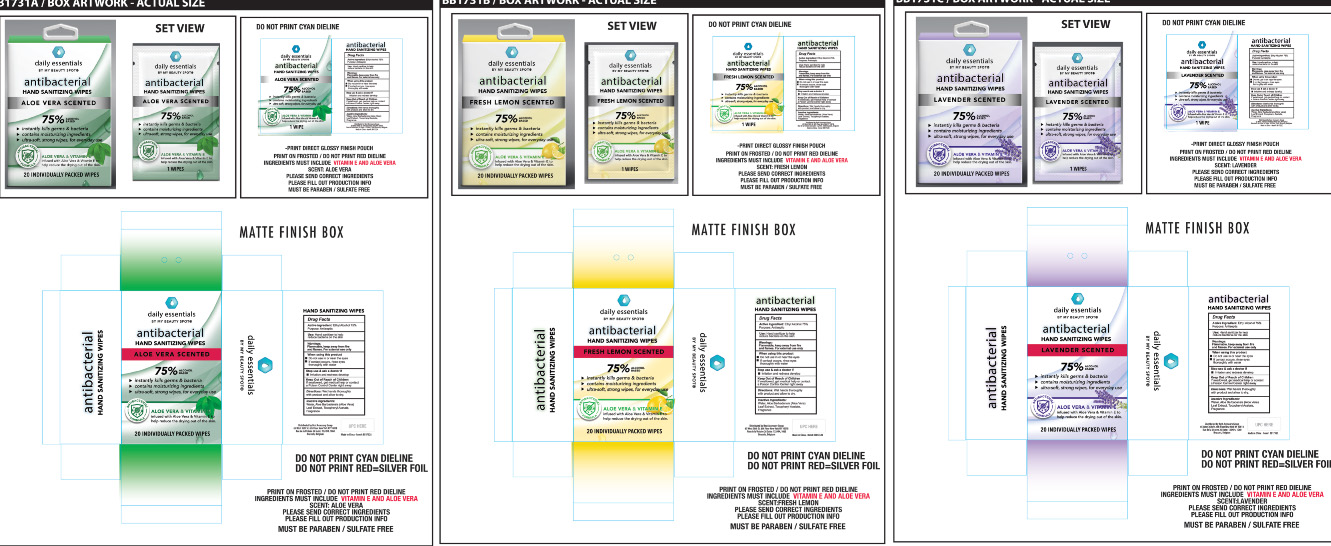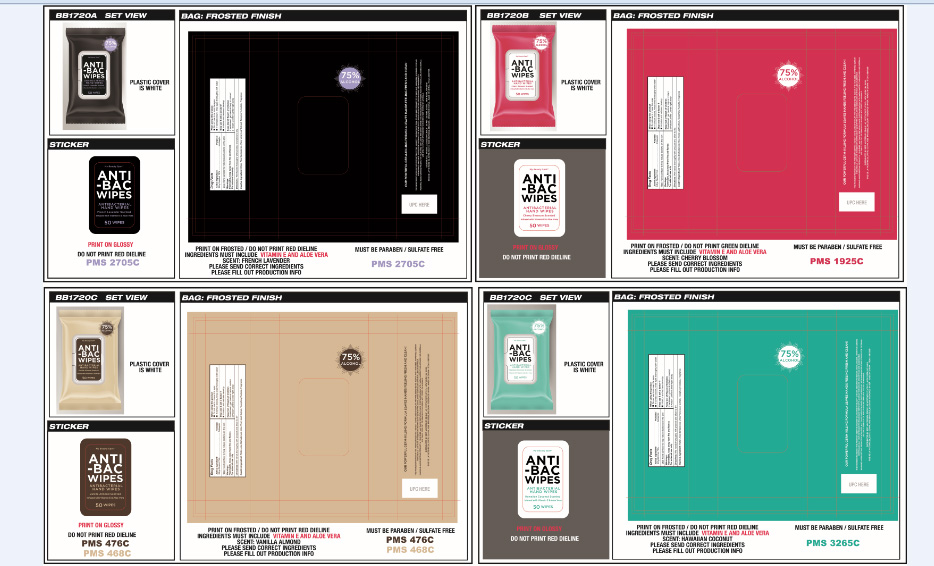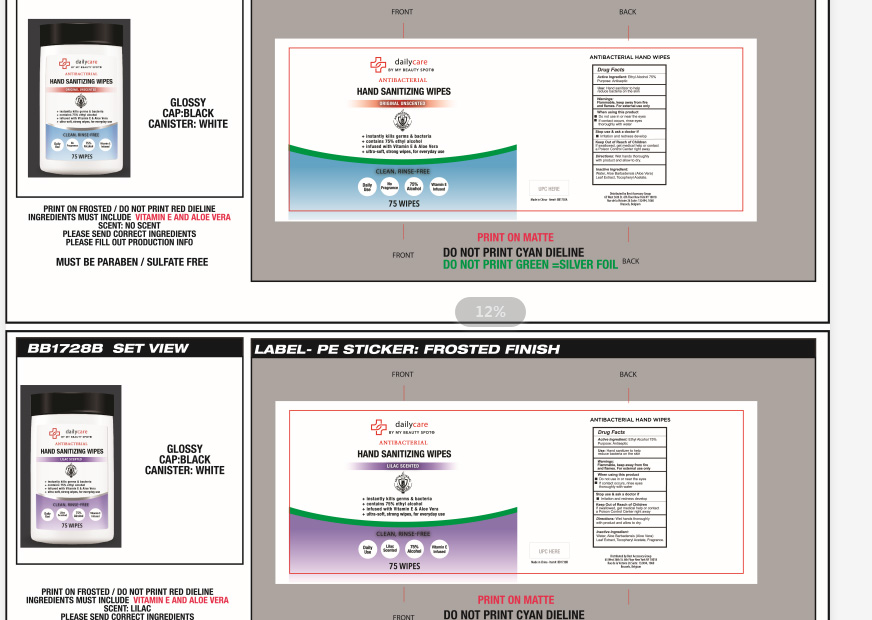 DRUG LABEL: WET WIPES
NDC: 78936-001 | Form: SWAB
Manufacturer: Hangzhou Caring Cleaning Commodity Co.,Ltd
Category: otc | Type: HUMAN OTC DRUG LABEL
Date: 20200611

ACTIVE INGREDIENTS: ALCOHOL 75 g/100 g
INACTIVE INGREDIENTS: ALOE VERA LEAF; ALPHA-TOCOPHEROL ACETATE; WATER

WET WIPES

Active Ingredient(s)

Ethyl Alcohol 75% v/v. Purpose: Antiseptic

Purpose

Antiseptic

Use

Decreases bacteria on skin. Recommended for repeated use

Warnings

For external use only. Flammable, keep product away from fire or flame.

Do not use over large areas of the body if you are allergic to any of the ingredients when using this product,avoid contact with eyes and face.If contact occurs,flush thoroughly with water.Stop use and ask a doctor if irritation or rash develops and continues for more than 72 hours.

Do not use

- in children less than 2 months of age
- on open skin wounds

Stop use and ask a doctor if irritation or rash occurs. These may be signs of a serious condition.

Keep out of reach of children. If swallowed, get medical help or contact a Poison Control Center right away.

Directions

For adults and children of 2 years and over.children under 2 years ask a doctor before use.

Wet hands thoroughly with product and allow to dry without wiping.

Inactive ingredients

Water,Aloe Barbadensis Leaf Extract,Tocopheryl Acetate

Package Label - Principal Display Panel

20 PCS IN 1 BOX NDC: 78936-001-01

50 PCS IN 1 BAG NDC: 78936-001-02

75 PCS IN 1 PAIL NDC: 78936-001-03